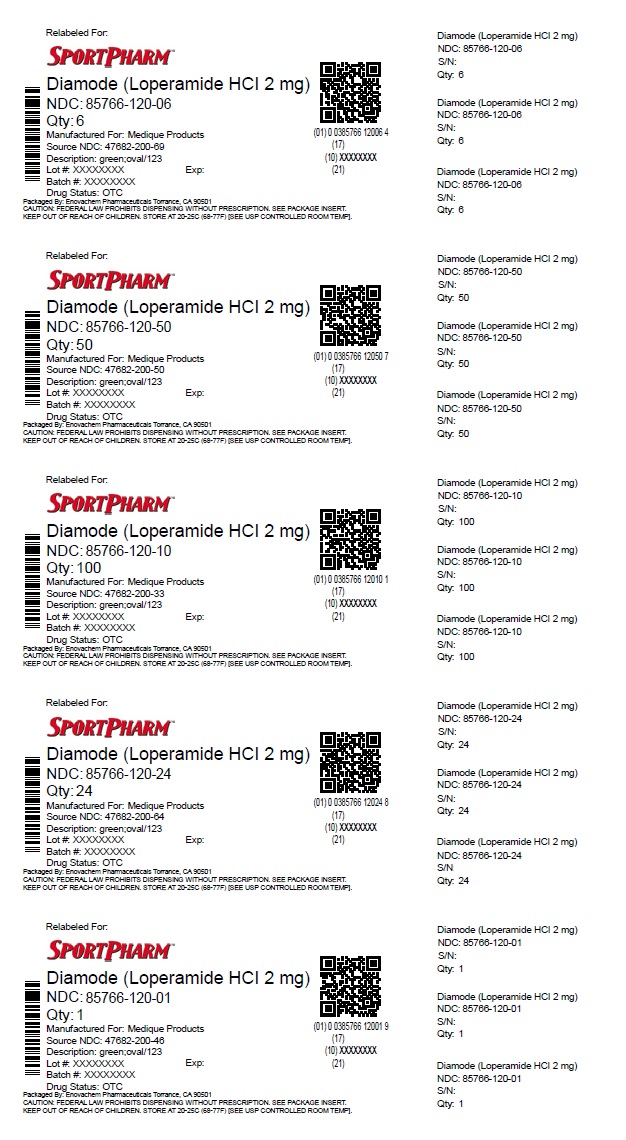 DRUG LABEL: MEDIQUE Diamode
NDC: 85766-120 | Form: TABLET
Manufacturer: Sportpharm, Inc. dba Sportpharm
Category: otc | Type: HUMAN OTC DRUG LABEL
Date: 20251211

ACTIVE INGREDIENTS: LOPERAMIDE HYDROCHLORIDE 2 mg/1 1
INACTIVE INGREDIENTS: ANHYDROUS LACTOSE; CROSPOVIDONE; D&C YELLOW NO. 10; FD&C BLUE NO. 1; MAGNESIUM STEARATE; POWDERED CELLULOSE; STARCH, CORN; CROSCARMELLOSE SODIUM

MEDIQUE® Diamode

Drug Facts

Active ingredient (in each caplet)

Loperamide Hydrochloride 2mg

Purpose

Antidiarrheal

Uses

Controls the symptoms of diarrhea, including Travelers diarrhea.

Warnings

Allergy alert:Do not use if you have ever had a rash or other allergic reaction to Loperamide HCl

Do not use

- if you have bloody or black stool

Ask a doctor before use if you have

- a fever
- mucus in stool
- a history of liver disease

Ask a doctor or pharmacist before use if you are

- taking antibiotics

When using this product

- tiredness, drowsiness or dizziness may occur
- be careful when driving or operating machinery

Stop use and ask a doctor if

- symptoms get worse
- diarrhea lasts more than 2 days
- you get abdominal swelling or bulging. These may be signs of a serious condition.

PREGNANCY OR BREAST FEEDING

If you are pregnant or breast feeding, ask a health professional before use.

KEEP OUT OF REACH OF CHILDREN

Keep this and all drugs out of the reach of children. In case of accidental overdose, contact a physician or Poison Control Center right away.

Directions

- do not use more than directed
- drink plenty of clear fluids to help prevent dehydration caused by diarrhea

Adults and children (12 years and older):Take 2 caplets after the first loose stool followed by 1 caplet after each subsequent loose stool but no more than 4 caplets in 24 hours.

Children under 12 years:Do not give to children under 12 years of age.

Other information

- store between 68º - 77ºF (20º - 25ºC)
- tamper-evident sealed packets
- do not use any opened or torn packet

Inactive ingredients

anhydrous lactose, croscarmellose sodium, crospovidone, D&C Yellow # 10, FD&C Blue # 1, hydrogenated vegetable oil, magnesium stearate, powdered cellulose, pregelatinized starch